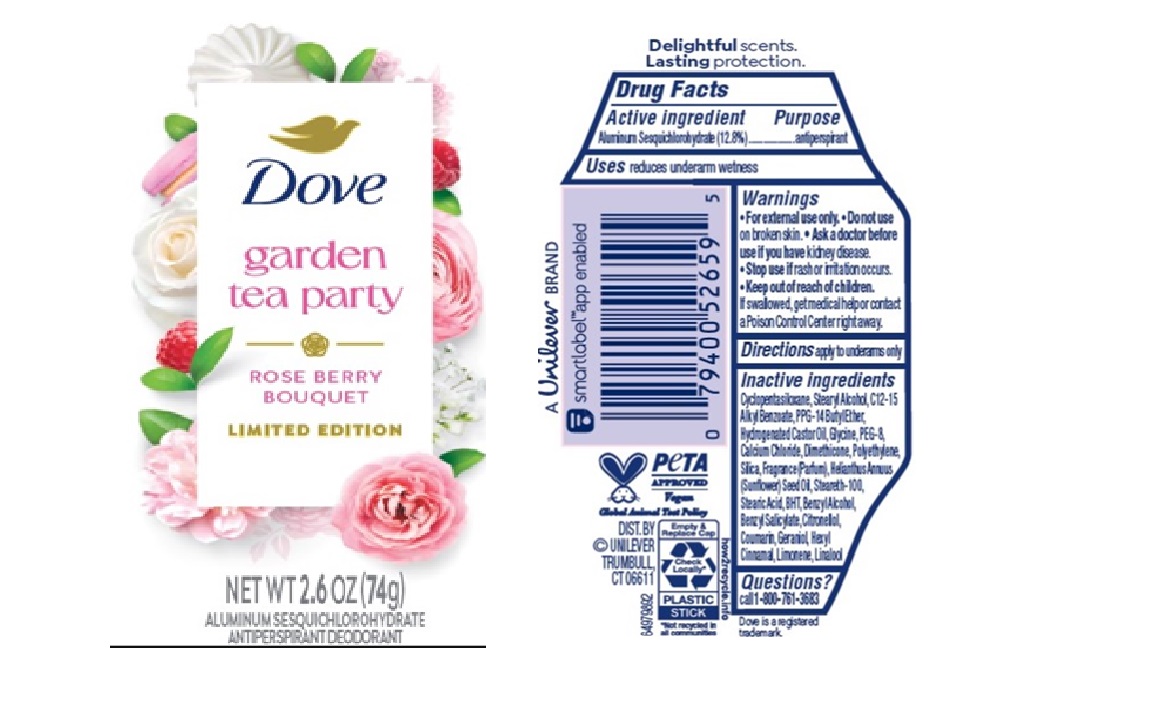 DRUG LABEL: Dove
NDC: 64942-2371 | Form: STICK
Manufacturer: Conopco d/b/a Unilever
Category: otc | Type: HUMAN OTC DRUG LABEL
Date: 20250501

ACTIVE INGREDIENTS: ALUMINUM SESQUICHLOROHYDRATE 12.8 g/100 g
INACTIVE INGREDIENTS: PPG-14 BUTYL ETHER; BENZYL ALCOHOL; SILICON DIOXIDE; PEG-8; STEARETH-100; LINALOOL; STEARYL ALCOHOL; DIMETHICONE; BENZYL SALICYLATE; GERANIOL; CYCLOPENTASILOXANE; BHT; POLYETHYLENE; HELIANTHUS ANNUUS (SUNFLOWER) SEED OIL; HEXYL CINNAMAL; C12-15 ALKYL BENZOATE; STEARIC ACID; CITRONELLOL; CALCIUM CHLORIDE; COUMARIN; HYDROGENATED CASTOR OIL; GLYCINE; LIMONENE, (+)-

Dove Garden Tea Party Rose Berry Bouquet Limited Edition Antiperspirant

DESCRIPTION

Dove Garden Tea Party Rose Berry Bouquet Limited Edition Antiperspirant

ACTIVE INGREDIENT

ALUMINUM SESQUICHLOROHYDRATE (12.8%)

PURPOSE

antiperspirant

INDICATIONS AND USAGE

reduces underarm wetness

WARNINGS

For external use only.
Do not use on broken skin.
Ask a doctor before use if you have kidney disease.
Stop use if rash or irritation occurs.

Keep out of reach of children. If swallowed, get medical help or contact a Poison Control Center right away

DOSAGE AND ADMINISTRATION

apply to underarms only

INACTIVE INGREDIENT

Cyclopentasiloxane, Stearyl Alcohol, C12 -15 Alkyl Benzoate, PPG-14 Butyl Ether, Hydrogenated Castor Oil, Glycine, PEG -8, Calcium Chloride, Dimethicone, Polyethylene, Silica, Fragrance (Parfum), Helianthus Annuus (Sunflower) Seed Oil, Steareth -100, Stearic Acid, BHT, Benzyl Alcohol, Benzyl Salicylate, Citronellol, Coumarin, Geraniol, Hexyl Cinnamal, Limonene, Linalool

QUESTIONS

Call 1-800-761-3683